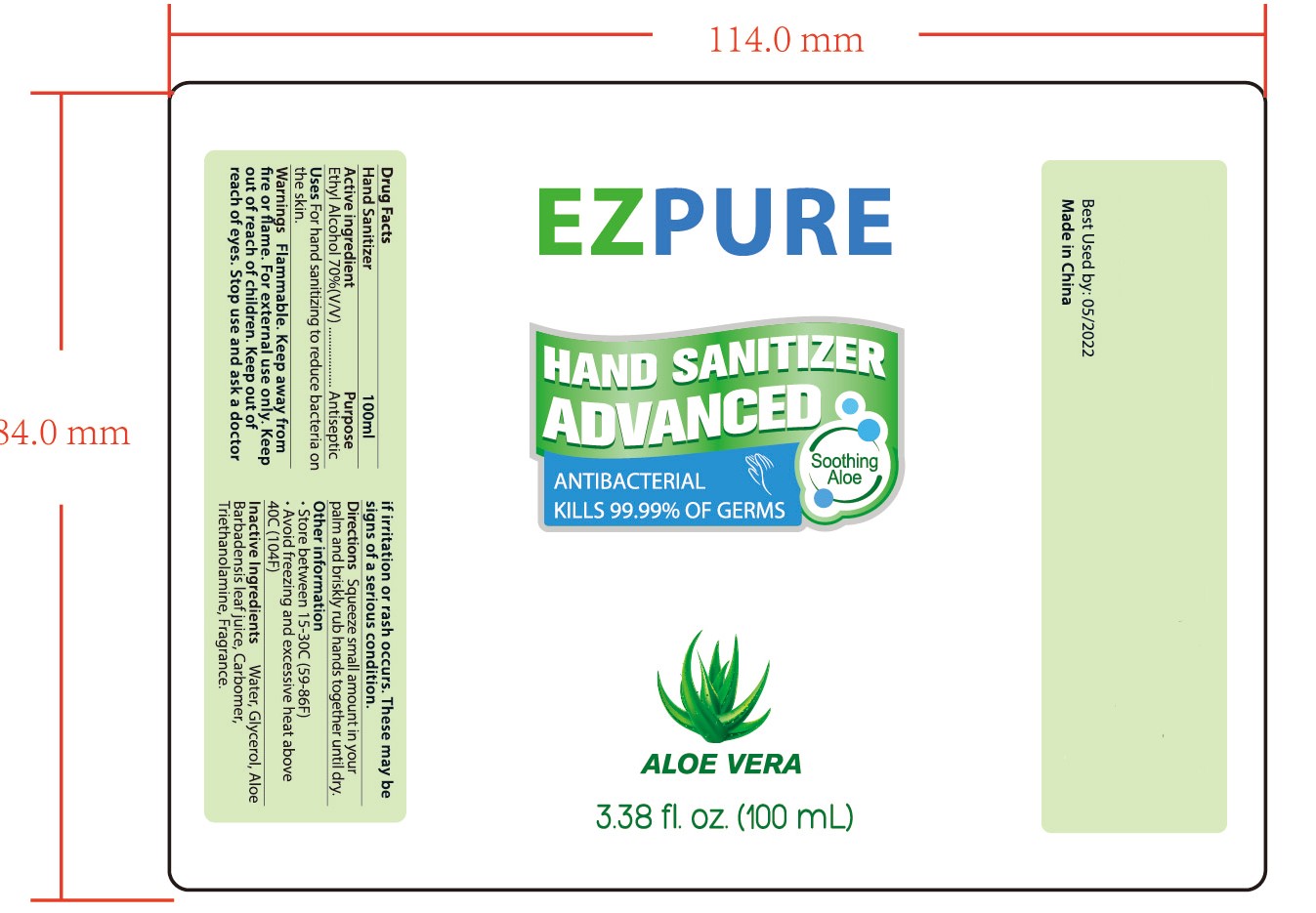 DRUG LABEL: HAND SANITIZER
NDC: 47993-242 | Form: GEL
Manufacturer: NINGBO JIANGBEI OCEAN STAR TRADING CO.,LTD
Category: otc | Type: HUMAN OTC DRUG LABEL
Date: 20201104

ACTIVE INGREDIENTS: ALCOHOL 70 mL/100 mL
INACTIVE INGREDIENTS: CARBOMER 940; ALOE VERA LEAF; WATER; GLYCERIN; TRIETHANOLAMINE BENZOATE

47993-242

Active ingredients

Ethyl Alcohol 70%（V/V）

PURPOSE

Antiseptic

Warnings:

Flammable. Keep away from fire or flame. For external use only. Keep out of reach of children. Keep out of reach of eyes.

Keep out of reach of children

Stop use and ask a doctor if irritation or rash occurs. These may be signs of a serious condition.

Uses：

For hand sanitizing to reduce bacteria on the skin.

Directions:

Squeeze small amount in your palm and briskly rub hands together until dry.

Other information

Store between 15-30℃（59-86℉）
Avoid freezing and excessive heat above 40℃（104℉）

Inactive Ingredients:

Water,Glycerin,Aloe Barbadensis Leaf Juice,Carbomer,Triethanolamine,Fragrance